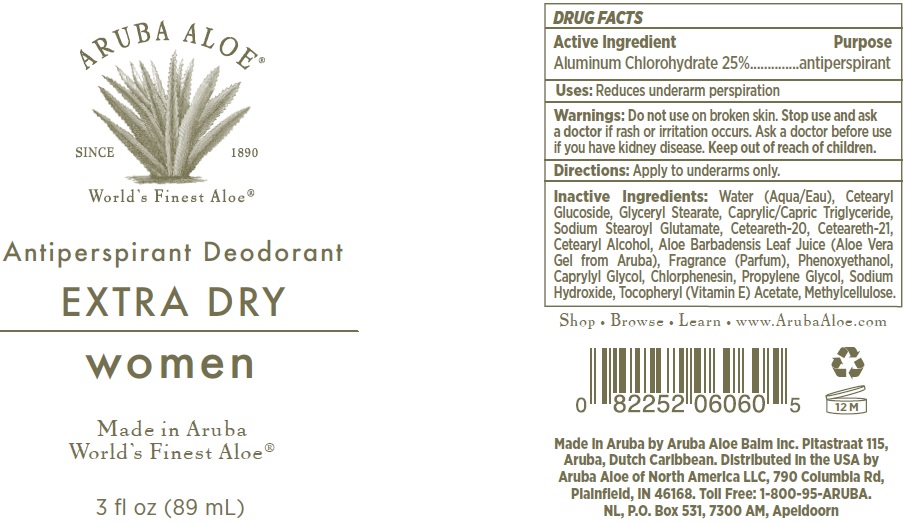 DRUG LABEL: Antiperspirant Deodorant Extra Dry Women
NDC: 53675-201 | Form: LOTION
Manufacturer: Aruba Aloe Balm NV
Category: otc | Type: HUMAN OTC DRUG LABEL
Date: 20231106

ACTIVE INGREDIENTS: ALUMINUM CHLOROHYDRATE 250 mg/1 mL
INACTIVE INGREDIENTS: GLYCERYL STEARATE SE; WATER; CETEARYL GLUCOSIDE; GLYCERYL MONOSTEARATE; MEDIUM-CHAIN TRIGLYCERIDES; SODIUM STEAROYL GLUTAMATE; POLYOXYL 20 CETOSTEARYL ETHER; CETOSTEARYL ALCOHOL; ALOE VERA LEAF; PHENOXYETHANOL; CAPRYLYL GLYCOL; CHLORPHENESIN; PROPYLENE GLYCOL; SODIUM HYDROXIDE; .ALPHA.-TOCOPHEROL ACETATE; METHYLCELLULOSE, UNSPECIFIED

Antiperspirant Deodorant Extra Dry Women

Active Ingredient

Aluminum Chlorohydrate 25%

Purpose

antiperspirant

Uses:

Reduces underarm perspiration

Warnings:

Do not use

on broken skin.

Stop use and ask a doctor

if rash or irritation occurs.

Ask a doctor before use

if you have kidney disease.

Directions:

Apply to underarms only.

Inactive Ingredients:

Water (Aqua/Eau), Cetearyl Glucoside, Glyceryl Stearate, Caprylic/Capric Triglyceride, Sodium Stearoyl Glutamate, Ceteareth-20, Ceteareth-21, Cetearyl Alcohol, Aloe Barbadensis Leaf Juice (Aloe Vera Gel from Aruba), Fragrance (Parfum), Phenoxyethanol, Caprylyl Glycol, Chlorphenesin, Propylene Glycol, Sodium Hydroxide, Tocopheryl (Vitamin E) Acetate, Methylcellulose.